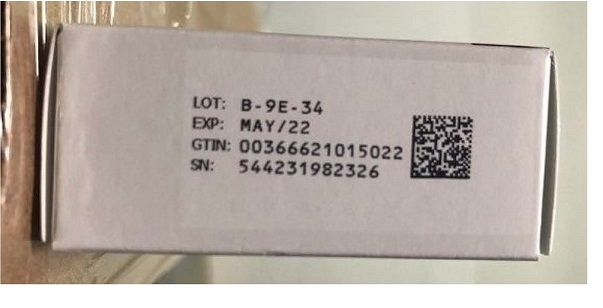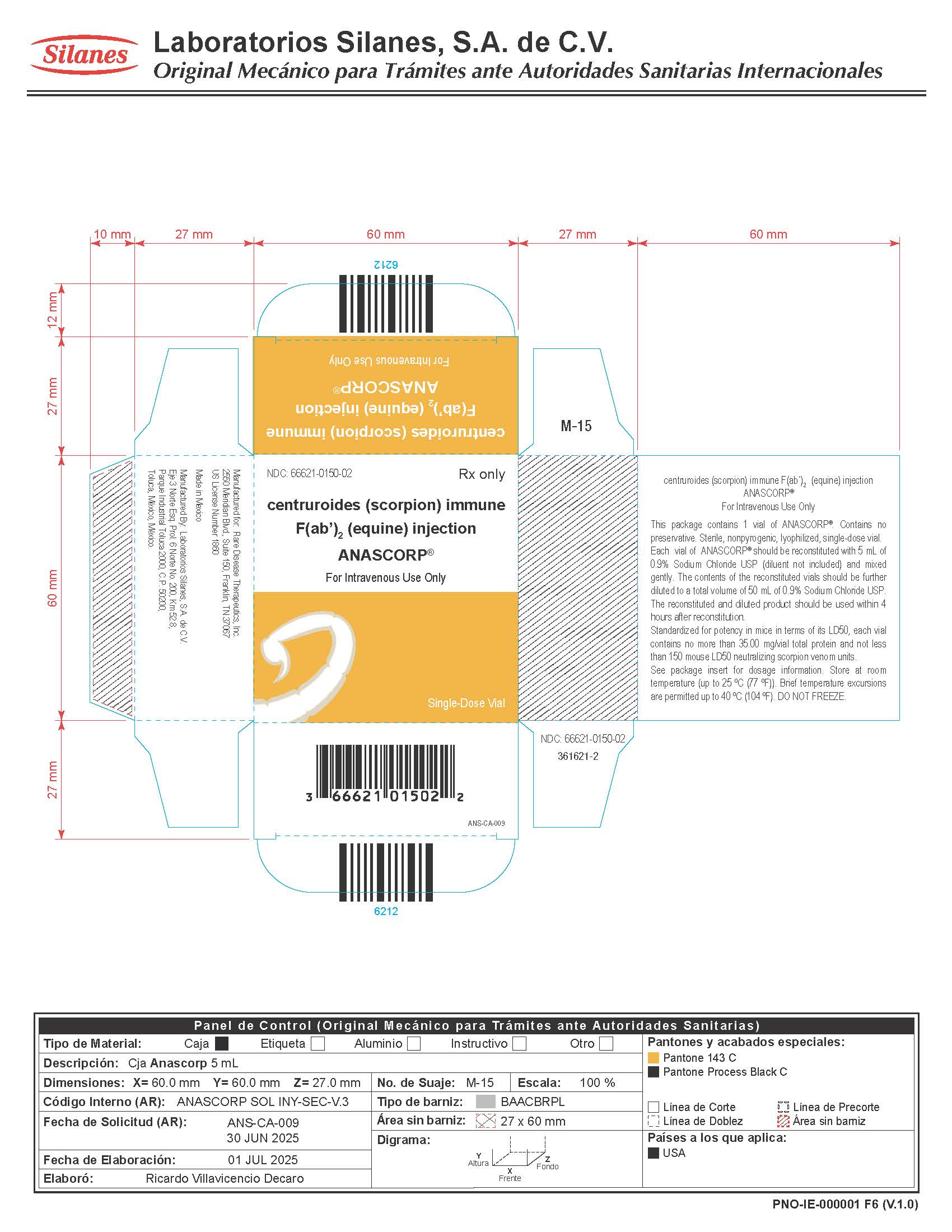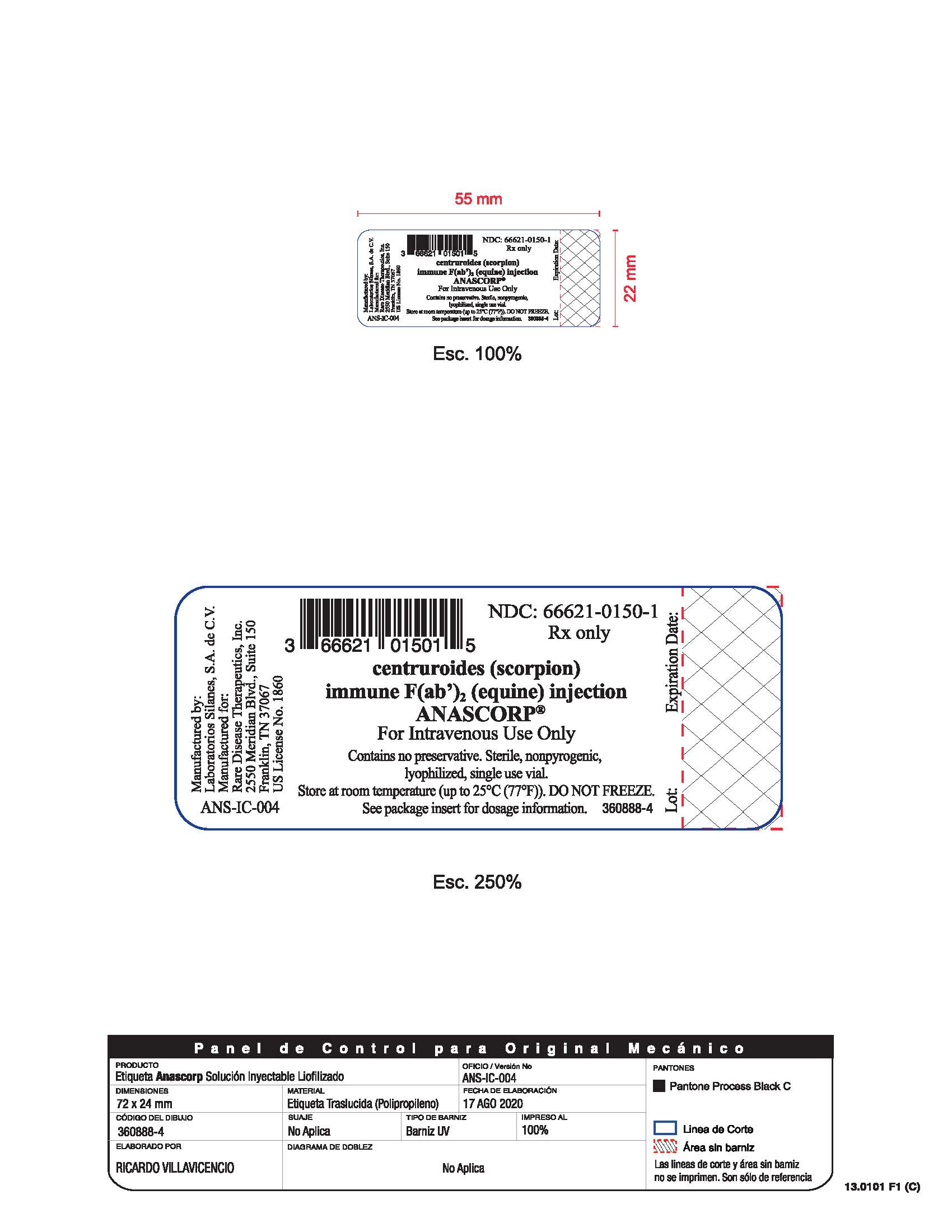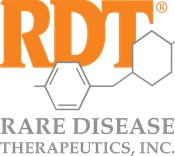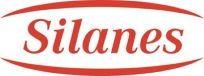 DRUG LABEL: ANASCORP
NDC: 66621-0150 | Form: INJECTION, POWDER, LYOPHILIZED, FOR SOLUTION
Manufacturer: Rare Disease Therapeutics, Inc
Category: other | Type: PLASMA DERIVATIVE
Date: 20250716

ACTIVE INGREDIENTS: CENTRUROIDES FAB2 ANTIVENIN (EQUINE) 7.0 mg/1 mL

HIGHLIGHTS OF PRESCRIBING INFORMATION

These highlights do not include all the information needed to use ANASCORP safely and effectively. See full prescribing information for ANASCORP.
ANASCORP®
centruroides (scorpion) immune F(ab')2 (equine)
injection
Lyophilized for Solution
For Intravenous Use Only
Initial U.S. Approval: 2011

1 INDICATIONS AND USAGE

- ANASCORP is an antivenin indicated for the treatment of clinical signs of scorpion envenomation. (1)

2 DOSAGE AND ADMINISTRATION

Intravenous use only.

Initial Dose | 3 vials | - Reconstitute each vial with 5 milliliters of sterile normal saline (0.9% NaCl). - Combine and further dilute to a total of 50 milliliters. - Infuse intravenously over 10 minutes.
Additional dose (s) | As needed | - Administer one vial at a time at 30-60 minute intervals. - Dilute to a total of 50 milliliters with sterile normal saline (0.9% NaCl). - Infuse intravenously over 10 minutes.

- Initiate treatment with ANASCORP as soon as possible after scorpion sting in patients who develop clinically important signs of scorpion envenomation, including but not limited to loss of muscle control, roving or abnormal eye movements, slurred speech, respiratory distress, excessive salivation, frothing at the mouth, vomiting.(2)
- Close patient monitoring is necessary.(2)

3 DOSAGE FORMS AND STRENGTHS

- Each vial contains a sterile, lyophilized preparation containing not more than 35 milligrams total protein and not less than 150 LD50 (mouse) neutralizing units.(3)

4 CONTRAINDICATIONS

None (4)

5 WARNINGS AND PRECAUTIONS

- Severe hypersensitivity reactions, including anaphylaxis, are possible with ANASCORP. Prepare for monitoring and management of allergic reactions, particularly in patients with a history of hypersensitivity to equine (horse) proteins or patients who have received previous therapy with antivenoms containing scorpion or equine proteins.(5.1)
- Delayed allergic reactions (serum sickness) may occur following treatment with ANASCORP. Patient monitoring with follow-up visit is recommended.(5.2)
- ANASCORP is made from equine plasma and may contain infectious agents, e.g. viruses.(5.3)
- Localized reactions and generalized myalgias have been reported with the use of cresol as an injectable excipient.(5.4)

6 ADVERSE REACTIONS

The most common adverse reactions observed in ≥ 2% of patients in the clinical studies for ANASCORP were: vomiting, pyrexia, rash, nausea and pruritus.(6)
To report SUSPECTED ADVERSE REACTIONS, contact Rare Disease Therapeutics, Inc., at 1 844-472-7389, or FDA at 1-800-FDA-1088 or www.fda.gov/medwatch.

8 USE IN SPECIFIC POPULATIONS

Pregnancy: No human or animal data. Use only if clearly needed.(8.1)

FULL PRESCRIBING INFORMATION

1 INDICATIONS AND USAGE

ANASCORP® [centruroides (scorpion) immune F(ab')2 (equine) injection] is an equine-derived antivenom indicated for treatment of patients with clinical signs of scorpion envenomation.

2 DOSAGE AND ADMINISTRATION

For Intravenous use only.

Initiate treatment with ANASCORP as soon as possible after scorpion sting in patients who develop clinically important signs of scorpion envenomation, including but not limited to loss of muscle control, roving or abnormal eye movements, slurred speech, respiratory distress, excessive salivation, frothing at the mouth and vomiting.(2)

Initial Dose: 3 vials

- The initial dose of ANASCORP is 3 vials.
- Reconstitute the contents of each vial with 5 milliliters of sterile normal saline (0.9% NaCl) and mix by continuous gentle swirling.
- Combine the contents of the reconstituted vials promptly and further dilute to a total volume of 50 milliliters with sterile normal saline (0.9% NaCl).
- Inspect the solution visually for particulate matter and discoloration prior to administration. Do not use if turbid.
- Infuse intravenously over 10 minutes.
- Monitor patient closely during and up to 60 minutes following the completion of infusion to determine if clinically important signs of envenomation have resolved.
- Discard partially used vials.

Additional Dosing

- Additional doses may be used if needed.
- Infuse one vial at a time at intervals of 30 to 60 minutes.
- Reconstitute the contents with 5 milliliters of sterile normal saline (0.9% NaCl) and mix by continuous gentle swirling.
- Further dilute to a total volume of 50 milliliters with sterile normal saline (0.9% NaCl). Inspect the solution visually for particulate matter or discoloration prior to administration.
- Infuse intravenously over 10 minutes.
- Monitor patient closely during and up to 60 minutes following the completion of infusion to determine if clinically important signs of envenomation have resolved.
- Discard partially used vials.

3 DOSAGE FORMS AND STRENGTHS

Each vial of ANASCORP contains a sterile, lyophilized preparation containing not more than 35 milligrams total protein and not less than 150 LD50 (mouse) neutralizing units.

4 CONTRAINDICATIONS

None.

5 WARNINGS AND PRECAUTIONS

5.1 Hypersensitivity Reactions

Severe hypersensitivity reactions, including anaphylaxis, may occur with ANASCORP. Close patient monitoring for hypersensitivity reactions and readiness with intravenous therapy using epinephrine, corticosteroids, and diphenhydramine hydrochloride is recommended during the infusion of ANASCORP. If an anaphylactic reaction occurs during the infusion, terminate administration at once and administer appropriate emergency medical care.
Patients with known allergies to horse protein are particularly at risk for an anaphylactic reaction. Patients who have had previous therapy with ANASCORP or another equine antivenom/antitoxin may have become sensitized to equine protein and be at risk for a severe hypersensitivity reaction.

5.2 Delayed Allergic Reactions (Serum Sickness)

Monitor patients with follow-up visit(s) for signs and symptoms of delayed allergic reactions or serum sickness (e.g., rash, fever, myalgia, arthralgia), and treat appropriately if necessary. Eight out of 1,534 (0.5%) patients in the clinical trials exhibited symptoms suggestive of serum sickness. (6.1)

5.3 Transmissible Infectious Agents

ANASCORP is made from equine (horse) plasma, it may therefore carry a risk of transmitting infectious agents, e.g., viruses.

5.4 Reaction to Cresol

Trace amounts of cresol from the manufacturing process are contained in ANASCORP. Localized reactions and generalized myalgias have been reported with the use of cresol as an injectable excipient.

6 ADVERSE REACTIONS

The most common adverse reactions observed in ≥ 2% of patients in the clinical studies for ANASCORP were: vomiting, pyrexia, rash, nausea and pruritus.

6.1 Clinical Trials Experience

Because clinical trials are conducted under widely varying conditions, adverse reaction rates observed in the clinical trials of a drug cannot be directly compared to rates in the clinical trials of another drug and may not reflect the rates observed in clinical practice.
A total of 1534 patients were treated with ANASCORP, ranging from less than one month to 90 years old. The patient population was comprised of 802 males and 732 females. Patients were monitored for signs and symptoms of adverse reactions, including acute hypersensitivity reactions and serum sickness. Follow-up telephone interviews were conducted at 24 hours, 7 days, and 14 days after treatment to assess symptoms suggestive of ongoing venom effect, serum sickness, and any other adverse reactions.
Table 1 shows the adverse reactions occurring in patients across all clinical trials for ANASCORP. Twenty-seven percent (421/1534) of patients receiving ANASCORP reported at least one adverse reaction.

Table 1: Adverse Reactions Reported in ≥ 1% of Patients
ADVERSE REACTIONS | ANASCORP [n=1534] n(%)
Vomiting | 72 (4.7)
Pyrexia | 63 (4.1)
Rash | 41 (2.7)
Nausea | 32 (2.1)
Pruritus | 31 (2.0)
Headache | 29 (1.9)
Rhinorrhea | 28 (1.8)
Myalgia | 25 (1.6)
Fatigue | 24 (1.6)
Cough | 22 (1.4)
Diarrhea | 20 (1.3)
Lethargy | 17 (1.1)

No patients died or discontinued study participation for severe adverse reactions.
Eight patients were considered to have serum sickness (Type III hypersensitivity); no patient manifested the full serum sickness syndrome. Three patients were treated with systemic corticosteroids and five others received either no treatment or symptomatic therapy.
34 patients experienced a total of 39 severe adverse reactions such as respiratory distress, aspiration, hypoxia, ataxia, pneumonia, and eye swelling. It is not clear whether these adverse reactions were related to ANASCORP envenomation or a combination of both^2.

6.2 Postmarketing Experience

The following adverse reactions have been identified during post approval use of ANASCORP . Because these reactions are reported voluntarily from a population of uncertain size, it is not always possible to reliably estimate their frequency or establish a causal relationship to drug exposure.
Chest tightness, palpitations, rash and pruritus.

7 DRUG INTERACTIONS

No drug interaction studies have been conducted with ANASCORP.

8 USE IN SPECIFIC POPULATIONS

8.1 Pregnancy

Risk Summary
Animal reproduction studies have not been conducted with ANASCORP. It is also not known whether ANASCORP can cause fetal harm when administered to a pregnant woman or can affect reproduction capacity. ANASCORP should be given to a pregnant woman only if clearly needed.

8.2 Lactation

Risk Summary
It is not known whether ANASCORP is excreted in human breast milk. Because many drugs are excreted in human milk, caution should be exercised when ANASCORP is administered to a nursing woman.

8.4 Pediatric Use

Seventy-eight percent of the patients enrolled in the clinical studies were pediatrics subjects(1204/1534), with ages ranging from less than one month to 18.7 years of age. Patient age groups were as follows: < 2 years of age, 29%, 2 to 5 years, 37%, 5 to 18 years, 34%. The efficacy and safety of ANASCORP is comparable in pediatric and adult patients.

8.5 Geriatric Use

Specific studies in elderly patients have not been conducted, ANASCORP was administered to 77 patients over the age of 65 years with comparable efficacy and safety to the overall patient population.

11 DESCRIPTION

ANASCORP [centruroides (scorpion) immune F(ab')2 (equine) injection] is a sterile nonpyrogenic, lyophilized, polyvalent preparation of equine immune globulin F(ab')2 fragments, manufactured from plasma of horses immunized with with venom of C. noxius, C.l. limpidus, C.l. tecomanus, and C.s.suffusus. The product is obtained by pepsin digestion of horse plasma to remove the Fc portion of immune globulin, followed by fractionation and purification steps. The F(ab')2 content is not less than 85%, F(ab) content is not more than 7%, and the product contains less than 5% intact immunoglobulin. Each vial of ANASCORP contains 13.00-25.00 milligrams of sodium chloride, 27.00 - 52.00 milligrams of sucrose, and 61.00-102.00 milligrams of glycine as stabilizers. Trace amounts of pepsin, cresol (< 0.058 mg/vial), borates (< 1 mg/vial) and sulfates (< 1.7 mg/vial) may be present from the manufacturing process. Each vial contains no more than 35 milligrams of protein and will neutralize at least 150 LD50 of Centruroides scorpion venom in a mouse neutralization assay.
The manufacturing procedures that contribute to the reduction of risk of viral transmission include pepsin digestion, ammonium sulfate precipitation/heat treatment and nanofiltration.

12 CLINICAL PHARMACOLOGY

12.1 Mechanism of Action

ANASCORP is composed of venom-specific F(ab')2 fragments of immunoglobulin G (IgG) that bind and neutralize venom toxins, facilitating redistribution away from target tissues and elimination from the body.^1

12.3 Pharmacokinetics

Eight clinically healthy volunteers (6 males and 2 females, age: 17 to 26 years) received a bolus intravenous dose of 47.5 mg of centruroides (scorpion) immune F(ab’)2, (equine) injection. Blood samples were collected till 504 hours (21 days) and pharmacokinetic parameters were estimated by non-compartmental analysis which are summarized in Table 2.^3

Table 2. Pharmacokinetic parameters of scorpion antivenom
Parameters | Mean ± sd
AUC(0-∞)(µg•hr/mL) | 706 ± 352
Clearance (mL/hr) | 83.5 ± 38.4
Half-life (hrs) | 159 ± 57
Vss (liters) | 13.6 ± 5.4

14 CLINICAL STUDIES

The efficacy of ANASCORP was assessed in a prospective double-blind randomized placebo-controlled study, four open-label studies and one retrospective study in various treatment settings in the United States and Mexico, where scorpion envenomation is common. A total of 1534 patients ranging from less than one month to 90 years old were treated. The majority of patients (78%, 1204/1534) were pediatric, ranging from less than one month to 18.7 years of age. Male (52.3%) and female patients (47.7%) were equally represented. Treatment success was determined by resolution of clinically important signs of scorpion envenomation within four hours of starting infusion. The randomized placebo study enrolled 15 subjects, eight to the ANASCORP treated group and seven to the placebo. The symptom resolution success rate was 100% for the ANASCORP treated and 14.3% for the placebo group.
A retrospective hospital chart review provided historical data from envenomated patients (n=97) who did not receive antivenom but were treated with sedatives and supportive care for symptoms of envenomation. These data were used as a historical control for expected outcomes in the absence of antivenom treatment. The historical controls were pediatric patients admitted to two pediatric intensive care units between 1990 and 2003 for the treatment of scorpion envenomation with supportive care only. The proportion of patients that required intensive care support four hours after intensive care unit admission, and the overall duration of the intensive care support requirement were calculated.
Overall, 95-100% of patients were relieved of systemic signs associated with scorpion envenomation in less than four hours after initiating ANASCORP treatment. In the historical control database, only 3.1% of patients experienced relief of symptoms within 4 hours of hospital admission.
In 1396/1534 patients the mean time from start of ANASCORP infusion to resolution of clinical signs and symptoms of envenomation was 1.42 hours (0.2 to 20.5 hours). Pediatric patients generally experienced a slightly faster time to resolution (1.28 ± 0.8 hours) compared with that of adult patients (1.91 ±1.4 hours). The time to resolution of symptoms was not affected by use of sedatives (474 patients who received sedatives resolved in 1.49 ± 1.1 hours and 922 patients who did not receive sedatives resolved in 1.38 ± 0.9 hours).

15 REFERENCES

1. Krifi MN, Savin S, Debray M, Bon C, Ayeb ME, Choumet V. Pharmacokinetic studies of scorpion venom before and after antivenom immunotherapy. Toxicon, 2005; 45: 187–198.

2. Boyer LV, Theodorou AA, Berg RA, Mallie J. Antivenom for Critically Ill Children with Neurotoxicity from Scorpion Stings. N Engl J Med,2009;360:2090-8.

3. Vasquez H, Chavez-Haro A, Garcia-Ubbelohde W, et al., Pharmacokinetics of a F(ab’)2 scorpion antivenin in healthy human volunteers, Toxicon, 2005;46: 797-805.

16 HOW SUPPLIED/STORAGE AND HANDLING

ANASCORP is supplied as a sterile lyophilized preparation in a single-use vial. When reconstituted, each vial contains not more than 7.0 milligrams per milliliter of protein, and not less than 150 mouse LD50 neutralizing units.

Each carton NDC 66621-0150-2 contains 1 vial of ANASCORP NDC 66621-0150-1.

- Store at room temperature (up to 25 ºC (77 ºF)). Brief temperature excursions are permitted up to 40 ºC (104ºF).
- DO NOT FREEZE.
- Discard partially used vials.

17 PATIENT COUNSELING INFORMATION

Serious Allergic Reactions
Advise patients to contact the physician or emergency department immediately if they experience any signs and symptoms of delayed allergic reactions or serum sickness up to 14 days following hospital discharge. Symptoms include rash, pruritus, joint pain, arthralgia, fever, lymphadenopathy, and malaise [see Hypersensitivity Reactions (5.1)].

Manufactured by:
Laboratorios Silanes, S.A. de C.V.
Toluca, Estado de Mexico, Mexico
Silanes® and the Silanes logo are registered trademarks in Mexico of Laboratorios Silanes, S.A. de C.V.

Manufactured for:
Rare Disease Therapeutics, Inc.
2550 Meridian Blvd., Suite 150
Franklin, TN 37067
www.raretx.com
RDT® and the RDT logo are registered trademarks of Rare Disease Therapeutics, Inc.

U.S. License No. 1860

RDT Part No: ANS-PI-009
Silanes Part No. 360891-7

PACKAGE LABEL

Anascorp Carton label

Anascorp Vial label

Serialization Example of Anascorp Carton label